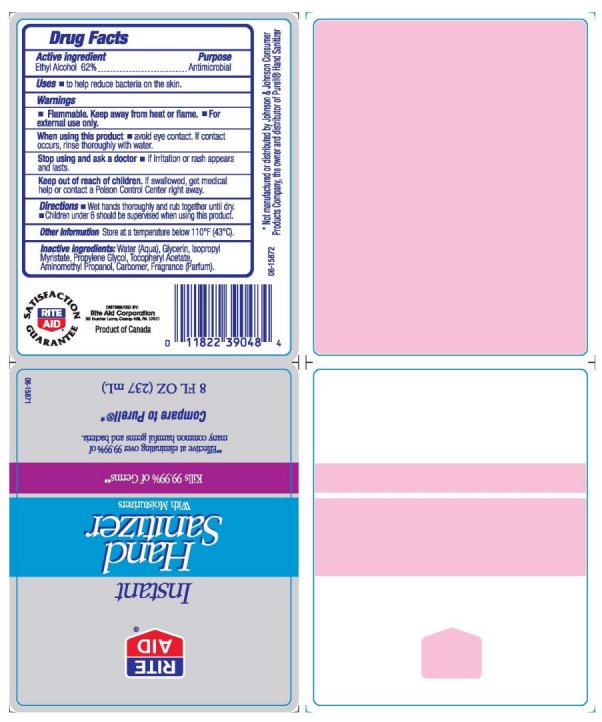 DRUG LABEL: Rite Aid Instant Hand Sanitizer With Moisturizers
NDC: 11822-1000 | Form: GEL
Manufacturer: Rite Aid Corporation
Category: otc | Type: HUMAN OTC DRUG LABEL
Date: 20091216

ACTIVE INGREDIENTS: ALCOHOL 62 mL/100 mL
INACTIVE INGREDIENTS: WATER; GLYCERIN; CARBOMER HOMOPOLYMER TYPE C; PROPYLENE GLYCOL; ISOPROPYL MYRISTATE; ALPHA-TOCOPHEROL ACETATE

Rite Aid Instant Hand Sanitizer With Moisturizers

Active Ingredient Purpose

Ethyl Alchohol 62 Percent Antiseptic

Uses

To help reduce bacteria on the skin.

Warnings

Flammable. Keep away from heat and flame. For external use only.

When using this product

Avoid eye contact. If contact occurs, rinse thoroughly with water.

Stop use and ask a doctor if skin irritation or rash appears and lasts.

Keep out of reach of children.

If swallowed, get medical help or contact a Poison Control Center right away.

Directions

Wet hands thoroughly and rub together until dry.

Children under 6 should be supervised when using this product.

Other information:

Store at a temperature below 110 degrees F (43 degrees C)

Questions? 1 800 632 6900

INACTIVE INGREDIENT

Inactive ingredients: Water aqua, Glycerin, Isopropyl Myristate, Propylene Glycol,

Tocopheryl Acetate, Aminomethyl Propanol, Carbomer, Fragrance Parfum

DESCRIPTION

Distributed By: Rite Aid Corporation 30 Hunter Lane Camp Hill PA 17011.

Distributed by:
Product of Canada
Not Manufactured or distributed by Johnson and Johnson Consumer Products Company, the owner and distributor of Purell Hand Sanitizer

PACKAGE LABEL

Rite Aid

Instant Hand Sanitizer With Moisturizers

Kills 99.99 percent of germs

Effective at eliminating over 99.99 percent of many common harmful germs and bacteria.

Compare to Purell

8 Fl OZ 236 ml